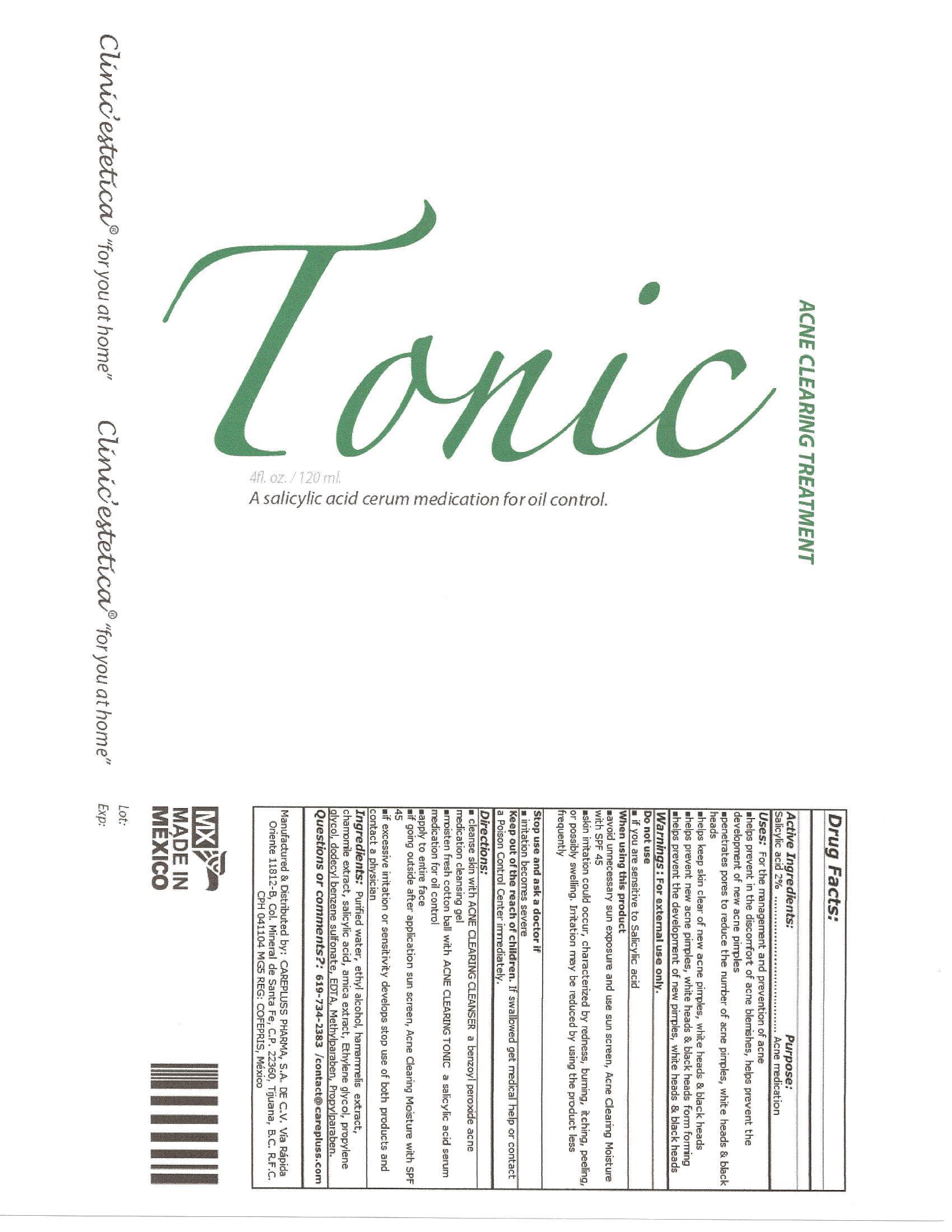 DRUG LABEL: Tonic
NDC: 51439-006 | Form: LIQUID
Manufacturer: CarePluss Pharma S.A. de C.V.
Category: otc | Type: HUMAN OTC DRUG LABEL
Date: 20130320

ACTIVE INGREDIENTS: SALICYLIC ACID .0024 mg/.120 mg
INACTIVE INGREDIENTS: DODECYLBENZENESULFONIC ACID; ALCOHOL; HAMAMELIS VIRGINIANA LEAF; CHAMAEMELUM NOBILE FLOWER; ARNICA MONTANA; ETHYLENE GLYCOL; VITAMIN A; PROPYLENE GLYCOL; DODECYLBENZENESULFONIC ACID; EDETIC ACID; METHYLPARABEN; PROPYLPARABEN

Active Ingredients: Purpose:
Salicylic acid 2%...........................................Acne medication

PURPOSE

Uses:For the management of acne

- helps clear up acne blemishes, black heads, helps prevent the development of new acne pimples
- penetrates pores to reduce the number of acne pimples, white heads and black heads
- help keep skin clear of new acne pimples, white heads and black heads
- helps prevent new acne pimples, white heads and black heads from forming
- help prevent the development of new pimples, white heads and black heads

Warnings: For external use only.
Do not use

- if you have sensitive skin and/or are sensitive to Salicylic acid

When using this product

- skin irritation and dryness is more likely to occur if you use another topical acne medication at the same time. If irritation occurs, only use one topical acne medication at a time
- avoid unnecessary sun exposure and use sun screen, Acne Clearing Moisture with SPF 45
- skin irritation may occur, characterized by redness, burning, itching, peeling, and possibly swelling. Irritation may be reduced by using the product less frequently or in a lower concentration

Stop use and ask a doctor if

- irritation becomes severe

Keep out of reach of children.If swallowed get medical help or contact a Poison Control center immediately.

Directions:

- cleanse skin with ACNE CLEARING CLEANSER a benzoyl peroxide acne medication cleansing gel.
- moisten fresh cotton ball with ACNE CLEARING TONIC a salicylic acid serum medication for oil control.
- apply on entire face.
- start with one application daily then gradually increase to 2 or 3.
- if going outside after cleansing apply sun screen, Acne Clearing Moisture with SPF 45
- if excessive irritation or sensitivity develops stop use of both products and contact a physician.

INACTIVE INGREDIENT

Ingredients: Purified Water, Ethyl Alcohol, Hamammelis Extract, Chamomile Extract, Salicyl Alcohol, Ethhylene Glycol, Propylene Glycol, Dodecyl Benzene Sulfonate, EDTA, Methylparaben, Propylparaben.

DOSAGE AND ADMINISTRATION

2 FL OZ / 60 ml

PACKAGE LABEL

Tonic
Acne Clearing Treatment